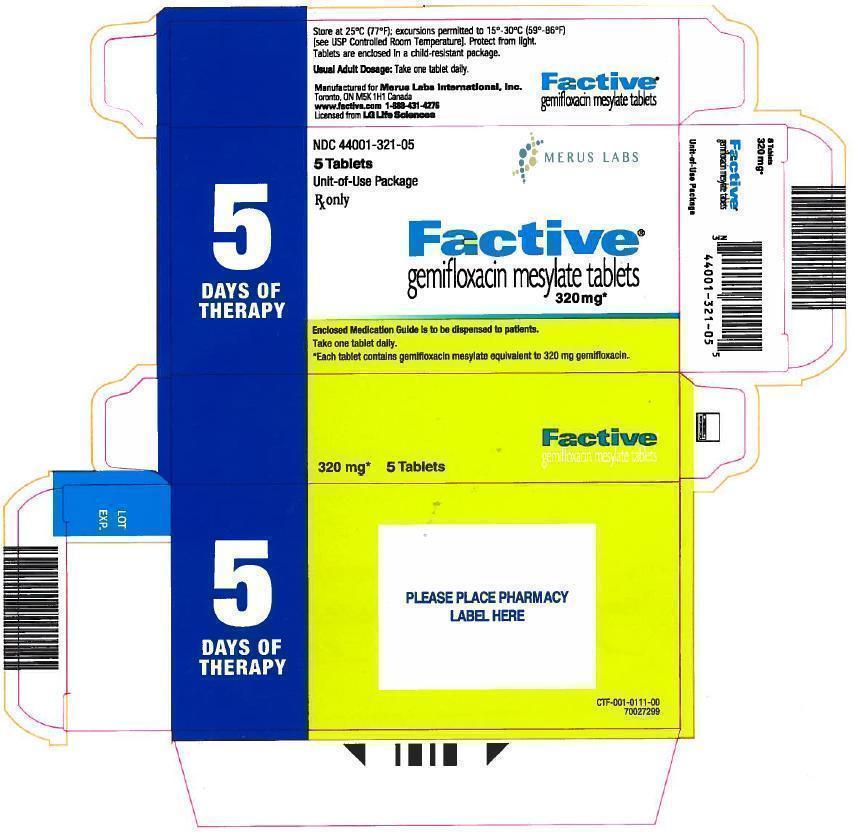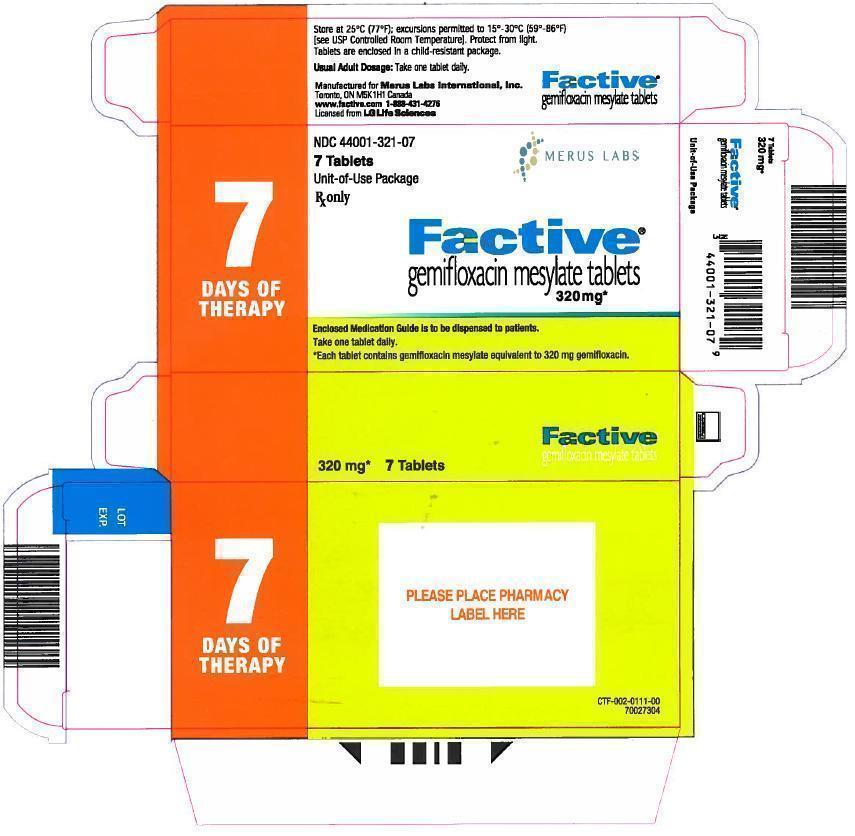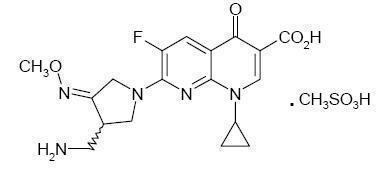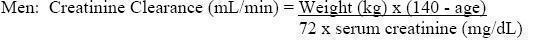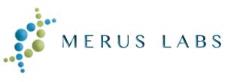 DRUG LABEL: FACTIVE
NDC: 44001-321 | Form: TABLET
Manufacturer: Merus Labs International Inc.
Category: prescription | Type: HUMAN PRESCRIPTION DRUG LABEL
Date: 20160801

ACTIVE INGREDIENTS: GEMIFLOXACIN MESYLATE 320 mg/1 1
INACTIVE INGREDIENTS: CROSPOVIDONE; MAGNESIUM STEARATE; CELLULOSE, MICROCRYSTALLINE; POVIDONE; TITANIUM DIOXIDE; HYPROMELLOSE 2910 (15 MPA.S); HYPROMELLOSE 2910 (5 MPA.S); POLYETHYLENE GLYCOL 4000; POLYETHYLENE GLYCOL 6000

FACTIVE ®
(gemifloxacin mesylate) Tablets

WARNING: SERIOUS ADVERSE REACTIONS INCLUDING TENDINITIS, TENDON RUPTURE, PERIPHERAL NEUROPATHY, CENTRAL NERVOUS SYSTEM EFFECTS AND EXACERBATION OF MYASTHENIA GRAVIS

Fluoroquinolones, including FACTIVE ® , have been associated with with disabling and potentially irreversible serious adverse reactions that have occurred together (See WARNINGS) including:

- Tendinitis and tendon rupture
- Peripheral neuropathy
- Central nervous system effects

Discontinue FACTIVE immediately and avoid the use of fluoroquinolones, including FACTIVE, in patients who experience any of these serious adverse reactions (See WARNINGS).

- Fluoroquinolones, including FACTIVE, may exacerbate muscle weakness in persons with myasthenia gravis. Avoid FACTIVE in patients with known history of myasthenia gravis (See WARNINGS).
- Because fluoroquinolones, including FACTIVE, have been associated with serious adverse reactions (See WARNINGS), reserve FACTIVE for use in patients who have no alternative treatment options for acute bacterial exacerbation of chronic bronchitis (See INDICATIONS AND USAGE).

To reduce the development of drug-resistant bacteria and maintain the effectiveness of FACTIVE and other antibacterial drugs, FACTIVE should be used only to treat infections that are proven or strongly suspected to be caused by bacteria.

DESCRIPTION

FACTIVE (gemifloxacin mesylate) is a synthetic broad-spectrum antibacterial agent for oral administration. Gemifloxacin, a compound related to the fluoroquinolone class of antibiotics, is available as the mesylate salt in the sesquihydrate form. Chemically, gemifloxacin is (R,S)-7-[(4Z)-3-(aminomethyl)-4-(methoxyimino)-1-pyrrolidinyl]-1-cyclopropyl-6-fluoro-1,4-dihydro-4-oxo-1,8-naphthyridine-3-carboxylic acid.

The mesylate salt is a white to light brown solid with a molecular weight of 485.49. Gemifloxacin is considered freely soluble at neutral pH (350 μg/mL at 37ºC, pH 7.0). Its empirical formula is C18H20FN5O4•CH4O3S and its chemical structure is:

Each white to off-white, oval, film-coated FACTIVE tablet has breaklines and GE 320 debossed on both faces and contains gemifloxacin mesylate equivalent to 320 mg gemifloxacin. The inactive ingredients are crospovidone, hydroxypropyl methylcellulose, magnesium stearate, microcrystalline cellulose, polyethylene glycol, povidone, and titanium dioxide.

CLINICAL PHARMACOLOGY

Pharmacokinetics

The pharmacokinetics of gemifloxacin are approximately linear over the dose range from 40 mg to 640 mg. There was minimal accumulation of gemifloxacin following multiple oral doses up to 640 mg a day for 7 days (mean accumulation <20%). Following repeat oral administration of 320 mg gemifloxacin once daily, steady-state is achieved by the third day of dosing.

Absorption and Bioavailability

Gemifloxacin, given as an oral tablet, is rapidly absorbed from the gastrointestinal tract. Peak plasma concentrations of gemifloxacin were observed between 0.5 and 2 hours following oral tablet administration and the absolute bioavailability of the 320 mg tablet averaged approximately 71% (95% CI 60%-84%). Following repeat oral doses of 320 mg to healthy subjects, the mean ± SD maximal gemifloxacin plasma concentrations (Cmax) and systemic drug exposure (AUC (0-24)) were 1.61 ± 0.51 μg/mL (range 0.70-2.62 μg/mL) and 9.93 ± 3.07 μg•hr/mL (range 4.71-20.1 μg•hr/mL), respectively. In patients with respiratory and urinary tract infections (n=1423), similar estimates of systemic drug exposure were determined using a population pharmacokinetics analysis (geometric mean AUC (0-24), 8.36 μg•hr/mL; range 3.2 – 47.7 μg•hr/mL).

The pharmacokinetics of gemifloxacin were not significantly altered when a 320 mg dose was administered with a high-fat meal. Therefore FACTIVE tablets may be administered without regard to meals.

Distribution

In vitro binding of gemifloxacin to plasma proteins in healthy subjects is approximately 60 to 70% and is concentration independent. After repeated doses, the in vivo plasma protein binding in healthy elderly and young subjects ranged from 55% to 73% and was unaffected by age. Renal impairment does not significantly affect the protein binding of gemifloxacin. The blood-to-plasma concentration ratio of gemifloxacin was 1.2:1. The geometric mean for Vdss/F is 4.18 L/kg (range, 1.66 – 12.12 L/kg).

Gemifloxacin is widely distributed throughout the body after oral administration. Concentrations of gemifloxacin in bronchoalveolar lavage fluid exceed those in the plasma. Gemifloxacin penetrates well into lung tissue and fluids. After five daily doses of 320 mg gemifloxacin, concentrations in plasma, bronchoalveolar macrophages, epithelial lining fluid and bronchial mucosa at approximately 2 hours were as in Table 1.

Table 1. Gemifloxacin Concentrations in Plasma and Tissues (320 mg Oral Dosing)

Tissue | Concentration (mean ± SD) | Ratio compared with plasma (mean ± SD)
Plasma | 1.40 (0.442) μg/mL | —
Bronchoalveolar Macrophages | 107 (77) μg/g | 90.5 (106.3)
Epithelial Lining Fluid | 2.69 (1.96) μg/mL | 1.99 (1.32)
Bronchial Mucosa | 9.52 (5.15) μg/g | 7.21 (4.03)

Metabolism

Gemifloxacin is metabolized to a limited extent by the liver. The unchanged compound is the predominant drug-related component detected in plasma (approximately 65%) up to 4 hours after dosing. All metabolites formed are minor (<10% of the administered oral dose); the principal ones are N-acetyl gemifloxacin, the E-isomer of gemifloxacin and the carbamyl glucuronide of gemifloxacin. Cytochrome P450 enzymes do not play an important role in gemifloxacin metabolism, and the metabolic activity of these enzymes is not significantly inhibited by gemifloxacin.

Excretion

Gemifloxacin and its metabolites are excreted via dual routes of excretion. Following oral administration of gemifloxacin to healthy subjects, a mean (± SD) of 61 ± 9.5% of the dose was excreted in the feces and 36 ± 9.3% in the urine as unchanged drug and metabolites. The mean (± SD) renal clearance following repeat doses of 320 mg was approximately 11.6 ± 3.9 L/hr (range 4.6-17.6 L/hr), which indicates active secretion is involved in the renal excretion of gemifloxacin. The mean (± SD) plasma elimination half-life at steady state following 320 mg to healthy subjects was approximately 7 ± 2 hours (range 4-12 hours).

Special Populations

Pediatric: The pharmacokinetics of gemifloxacin in pediatric subjects have not been studied.

Geriatric: In adult subjects, the pharmacokinetics of gemifloxacin are not affected by age.

Gender: There are no significant differences between gemifloxacin pharmacokinetics in males and females when differences in body weight are taken into account. Population pharmacokinetic studies indicated that following administration of 320 mg gemifloxacin, AUC values were approximately 10% higher in healthy female patients compared to males. Males and females had mean AUC values of 7.98 μg•hr/mL (range, 3.21 – 42.71 μg•hr/mL) and 8.80 μg•hr/mL (range, 3.33 – 47.73 μg•hr/mL), respectively. No gemifloxacin dosage adjustment based on gender is necessary.

Hepatic Insufficiency: The pharmacokinetics following a single 320 mg dose of gemifloxacin were studied in patients with mild (Child-Pugh Class A) to moderate (Child-Pugh Class B) liver disease. There was a mean increase in AUC (0-inf) of 34% and a mean increase in Cmax of 25% in these patients with hepatic impairment compared to healthy volunteers.

The pharmacokinetics of a single 320 mg dose of gemifloxacin were also studied in patients with severe hepatic impairment (Child-Pugh Class C). There was a mean increase in AUC (0-inf) of 45% and a mean increase in Cmax of 41% in these subjects with hepatic impairment compared to healthy volunteers.

These average pharmacokinetic increases are not considered to be clinically significant. There was no significant change in plasma elimination half-life in the mild, moderate or severe hepatic impairment patients. No dosage adjustment is recommended in patients with mild (Child-Pugh Class A), moderate (Child-Pugh Class B) or severe (Child-Pugh Class C) hepatic impairment. (See DOSAGE AND ADMINISTRATION .)

Renal Insufficiency: Results from population pharmacokinetic and clinical pharmacology studies with repeated 320 mg doses indicate the clearance of gemifloxacin is reduced and the plasma elimination is prolonged, leading to an average increase in AUC values of approximately 70% in patients with renal insufficiency. In the pharmacokinetic studies, gemifloxacin Cmax was not significantly altered in subjects with renal insufficiency. Dose adjustment in patients with creatinine clearance >40 mL/min is not required. Modification of the dosage is recommended for patients with creatinine clearance ≤40 mL/min. (See DOSAGE AND ADMINISTRATION .)

Hemodialysis removes approximately 20 to 30% of an oral dose of gemifloxacin from plasma.

Photosensitivity Potential

In a study of the skin response to ultraviolet and visible radiation conducted in 40 healthy volunteers, the minimum erythematous dose (MED) was assessed following administration of either gemifloxacin 160 mg once daily, gemifloxacin 320 mg once daily, ciprofloxacin 500 mg BID, or placebo for 7 days. At 5 of the 6 wavelengths tested (295-430 nm), the photosensitivity potential of gemifloxacin was not statistically different from placebo. At 365 nm (UVA region), gemifloxacin showed a photosensitivity potential similar to that of ciprofloxacin 500 mg BID and the photosensitivity potential for both drugs were statistically greater than that of placebo. Photosensitivity reactions were reported rarely in clinical trials with gemifloxacin (0.039%). (See ADVERSE REACTIONS.)

It is difficult to ascribe relative photosensitivity/phototoxicity among various fluoroquinolones during actual patient use because other factors play a role in determining a subject’s susceptibility to this adverse event such as: a patient’s skin pigmentation, frequency and duration of sun and artificial ultraviolet light (UV) exposure, wearing of sun screen and protective clothing, the use of other concomitant drugs and the dosage and duration of fluoroquinolone therapy. (See ADVERSE REACTIONS and ADVERSE REACTIONS: Post-Marketing Adverse Reactions.)

Drug-Drug Interactions

Antacids/Di- and Trivalent Cations: The systemic availability of gemifloxacin is significantly reduced when an aluminum- and magnesium- containing antacid is concomitantly administered (AUC decreased 85%; Cmax decreased 87%). Administration of an aluminum- and magnesium- containing antacid or ferrous sulfate (325 mg) at 3 hours before or at 2 hours after gemifloxacin did not significantly alter the systemic availability of gemifloxacin. Therefore, aluminum- and/or magnesium- containing antacids, ferrous sulfate (iron), multivitamin preparations containing zinc or other metal cations, or Videx® (didanosine) chewable/buffered tablets or the pediatric powder for oral solution should not be taken within 3 hours before or 2 hours after taking FACTIVE tablets.

Calcium carbonate (1000 mg) given either 2 hr before or 2 hr after gemifloxacin administration showed no notable reduction in gemifloxacin systemic availability. Calcium carbonate administered simultaneously with gemifloxacin resulted in a small, not clinically significant, decrease in gemifloxacin exposure [AUC (0-inf) decreased 21% and Cmax decreased].

Sucralfate: When sucralfate (2 g) was administered 3 hours prior to gemifloxacin, the oral bioavailability of gemifloxacin was significantly reduced (53% decrease in AUC; 69% decrease in Cmax). When sucralfate (2 g) was administered 2 hours after gemifloxacin, the oral bioavailability of gemifloxacin was not significantly affected; therefore FACTIVE should be taken at least 2 hours before sucralfate. (See PRECAUTIONS.)

In Vitro Metabolism: Results of in vitro inhibition studies indicate that hepatic cytochrome P450 (CYP450) enzymes do not play an important role in gemifloxacin metabolism. Therefore gemifloxacin should not cause significant in vivo pharmacokinetic interactions with other drugs that are metabolized by CYP450 enzymes.

Theophylline: Gemifloxacin 320 mg at steady-state did not affect the repeat dose pharmacokinetics of theophylline (300 to 400 mg BID to healthy male subjects).

Digoxin: Gemifloxacin 320 mg at steady-state did not affect the repeat dose pharmacokinetics of digoxin (0.25 mg once daily to healthy elderly subjects).

Oral Contraceptives: The effect of an oral estrogen/progesterone contraceptive product (once daily for 21 days) on the pharmacokinetics of gemifloxacin (320 mg once daily for 6 days) in healthy female subjects indicates that concomitant administration caused an average reduction in gemifloxacin AUC and Cmax of 19% and 12%. These changes are not considered clinically significant. Gemifloxacin 320 mg at steady-state did not affect the repeat dose pharmacokinetics of an ethinylestradiol/levonorgestrol oral contraceptive product (30 μg/150 μg once daily for 21 days to healthy female subjects).

Cimetidine: Co-administration of a single dose of 320 mg gemifloxacin with cimetidine 400 mg four times daily for 7 days resulted in slight average increases in gemifloxacin AUC(0-inf) and Cmax of 10% and 6%, respectively. These increases are not considered clinically significant.

Omeprazole: Co-administration of a single dose of 320 mg gemifloxacin with omeprazole 40 mg once daily for 4 days resulted in slight average increases in gemifloxacin AUC(0-inf) and Cmax of 10% and 11%, respectively. These increases are not considered clinically significant.

Warfarin: Administration of repeated doses of gemifloxacin (320 mg once daily for 7 days) to healthy subjects on stable warfarin therapy had no significant effect on warfarin-induced anticoagulant activity (i.e., International Normalized Ratios for Prothrombin Time). (See PRECAUTIONS: Drug Interactions.)

Probenecid: Administration of a single dose of 320 mg gemifloxacin to healthy subjects who also received repeat doses of probenecid (total dose = 4.5 g) reduced the mean renal clearance of gemifloxacin by approximately 50%, resulting in a mean increase of 45% in gemifloxacin AUC (0-inf) and a prolongation of mean half-life by 1.6 hours. Mean gemifloxacin Cmax increased 8%.

MICROBIOLOGY

Gemifloxacin has in vitro activity against a wide range of Gram-negative and Gram-positive microorganisms. Gemifloxacin is bactericidal with minimum bactericidal concentrations (MBCs) generally within one dilution of the minimum inhibitory concentrations (MICs). Gemifloxacin acts by inhibiting DNA synthesis through the inhibition of both DNA gyrase and topoisomerase IV (TOPO IV), which are essential for bacterial growth. Streptococcus pneumoniae showing mutations in both DNA gyrase and TOPO IV (double mutants) are resistant to most fluoroquinolones. Gemifloxacin has the ability to inhibit both enzyme systems at therapeutically relevant drug levels in S. pneumoniae (dual targeting), and has MIC values that are still in the susceptible range for some of these double mutants. However, the presence of double mutants was not evaluated in clinical trials; therefore, the clinical significance of these in vitro data are unknown.

The mechanism of action of quinolones, including gemifloxacin, is different from that of macrolides, beta-lactams, aminoglycosides, or tetracyclines; therefore, microorganisms resistant to these classes of drugs may be susceptible to gemifloxacin and other quinolones. There is no known cross-resistance between gemifloxacin and the above mentioned classes of antimicrobials.

The main mechanism of fluoroquinolone resistance is due to mutations in DNA gyrase and/or TOPO IV. Resistance to gemifloxacin develops slowly via multistep mutations and efflux in a manner similar to other fluoroquinolones. The frequency of spontaneous mutation is low (10^-7 to <10^-10). Although cross-resistance has been observed between gemifloxacin and other fluoroquinolones, some microorganisms resistant to other fluoroquinolones may be susceptible to gemifloxacin.

Gemifloxacin has been shown to be active against most strains of the following microorganisms, both in vitro and in clinical infections as described in the INDICATIONS AND USAGE section.

Aerobic Gram-positive microorganisms

Streptococcus pneumoniae (including multi-drug resistant strains [MDRSP])*

*MDRSP: multi-drug resistant Streptococcus pneumoniae, includes isolates previously known as PRSP (penicillin-resistant Streptococcus pneumoniae), and are strains resistant to two or more of the following antibiotics: penicillin (MIC ≥2 μg/mL), 2nd generation cephalosporins (e.g., cefuroxime), macrolides, tetracyclines and trimethoprim/sulfamethoxazole.

Aerobic Gram-negative microorganisms

Haemophilus influenzae

Haemophilus parainfluenzae
Klebsiella pneumoniae (many strains are only moderately susceptible)
Moraxella catarrhalis

Other microorganisms

Chlamydia pneumoniae

Mycoplasma pneumoniae

The following data are available, but their clinical significance is unknown.

Gemifloxacin exhibits in vitro minimal inhibitory concentrations (MICs) of 0.25 μg/mL or less against most (≥90%) strains of the following microorganisms; however, the safety and effectiveness of gemifloxacin in treating clinical infections due to these microorganisms has not been established in adequate and well-controlled clinical trials:

Aerobic Gram-positive microorganisms

Staphylococcus aureus (methicillin-susceptible strains only)
Streptococcus pyogenes

Aerobic Gram-negative microorganisms

Acinetobacter lwoffii

Klebsiella oxytoca

Legionella pneumophila

Proteus vulgaris

Susceptibility Tests

Dilution techniques: Quantitative methods are used to determine antimicrobial minimum inhibitory concentrations (MICs). These MICs provide estimates of the susceptibility of bacteria to antimicrobial compounds. The MICs should be determined using a standardized procedure. Standardized procedures are based on a dilution method^1 (broth or agar) or equivalent with standardized inoculum concentrations and standardized concentrations of gemifloxacin powder. The MICs should be interpreted according to the following criteria:

For testing Klebsiella pneumoniae:

MIC (µg/mL) | Interpretation
0.25 | Susceptible (S)
0.5 | Intermediate (I)
1.0 | Resistant (R)

For testing Haemophilus influenzae and Haemophilus parainfluenzaea:

MIC (µg/mL) | Interpretation
0.12 | Susceptible (S)

a This interpretive standard is applicable only to broth microdilution susceptibility testing with Haemophilus influenzae and Haemophilus parainfluenzae using Haemophilus Test Medium (HTM)^1.

The current absence of data on resistant strains precludes defining any results other than Susceptible. Strains yielding MIC results suggestive of a nonsusceptible category should be submitted to a reference laboratory for further testing.

For testing Streptococcus pneumoniaeb:

MIC (µg/mL) | Interpretation
0.12 | Susceptible (S)
0.25 | Intermediate (I)
0.5 | Resistant (R)

b These interpretive standards are applicable only to broth microdilution susceptibility tests using cation-adjusted Mueller-Hinton broth with 2-5% lysed horse blood.

A report of Susceptible indicates that the pathogen is likely to be inhibited if the antimicrobial compound in the blood reaches the concentration usually achievable. A report of Intermediate indicates that the result should be considered equivocal, and if the microorganism is not fully susceptible to alternative, clinically feasible drugs, the test should be repeated. This category implies possible clinical applicability in body sites where the drug is physiologically concentrated or in situations where high dosage of drug can be used. This category also provides a buffer zone, which prevents small uncontrolled technical factors from causing major discrepancies in interpretation. A report of Resistant indicates that the pathogen is not likely to be inhibited if the antimicrobial compound in the blood reaches the concentration usually achievable; other therapy should be selected.

Standardized susceptibility test procedures require the use of laboratory control microorganisms to control the technical aspects of the laboratory procedures. Standard gemifloxacin powder should provide the following MIC values:

Microorganism |  | MIC Range (µg/mL)
Escherichia coli | ATCC 25922 | 0.004-0.016
Haemophilus influenzae | ATCC 49247 | 0.002-0.008c
Streptococcus pneumoniae | ATCC 49619 | 0.008-0.03d

c This quality control range is applicable to only H. influenzae ATCC 49247 tested by a broth microdilution procedure using Haemophilus Test Medium (HTM)^1.

d This quality control range is applicable to only S. pneumoniae ATCC 49619 tested by a broth microdilution procedure using cation-adjusted Mueller-Hinton broth with 2-5% lysed horse blood.

Diffusion Techniques: Quantitative methods that require measurement of zone diameters also provide reproducible estimates of the susceptibility of bacteria to antimicrobial compounds. One such standardized procedure^2 requires the use of standardized inoculum concentrations. This procedure uses paper disks impregnated with 5 g gemifloxacin to test the susceptibility of microorganisms to gemifloxacin.

Reports from the laboratory providing results of the standard single-disk susceptibility test with a 5 g gemifloxacin disk should be interpreted according to the following criteria:

For testing Klebsiella pneumoniae:

Zone Diameter (mm) | Interpretation
20 | Susceptible (S)
16-19 | Intermediate (I)
15 | Resistant (R)

For testing Haemophilus influenzae and Haemophilus parainfluenzaee:

Zone Diameter (mm) | Interpretation
18 | Susceptible (S)

e This interpretive standard is applicable only to disk diffusion susceptibility testing with Haemophilus influenzae and Haemophilus parainfluenzae using Haemophilus Test Medium (HTM).^2

The current absence of data on resistant strains precludes defining any results other than Susceptible. Strains yielding zone diameter results suggestive of a nonsusceptible category should be submitted to a reference laboratory for further testing.

For testing Streptococcus pneumoniaef:

Zone Diameter (mm) | Interpretation
23 | Susceptible (S)
20-22 | Intermediate (I)
19 | Resistant (R)

f These zone diameter standards apply only to tests performed using Mueller-Hinton agar supplemented with 5% defibrinated sheep blood incubated in 5% CO2.

Interpretation should be as stated above for results using dilution techniques. Interpretation involves correlation of the diameter obtained in the disk test with the MIC for gemifloxacin.

As with standardized dilution techniques, diffusion methods require the use of laboratory control microorganisms that are used to control the technical aspects of the laboratory procedures. For the diffusion technique, the 5 g gemifloxacin disk should provide the following zone diameters in these laboratory quality control strains:

Microorganism |  | Zone Diameter (mm)
Escherichia coli | ATCC 25922 | 29-36
Haemophilus influenzae | ATCC 49247 | 30-37g
Streptococcus pneumoniae | ATCC 49619 | 28-34h

g This quality control range is applicable to only H. influenzae ATCC 49247 tested by a disk diffusion procedure using Haemophilus Test Medium (HTM)^2.

h This quality control range is applicable to only S. pneumoniae ATCC 49619 tested by a disk diffusion procedure using Mueller-Hinton agar supplemented with 5% defibrinated sheep blood and incubated in 5% CO2.

INDICATIONS AND USAGE

FACTIVE is indicated for the treatment of infections caused by susceptible strains of the designated microorganisms in the conditions listed below. (See DOSAGE AND ADMINISTRATION and CLINICAL STUDIES.)

Acute bacterial exacerbation of chronic bronchitis (ABECB) caused by Streptococcus pneumoniae, Haemophilus influenzae, Haemophilus parainfluenzae, or Moraxella catarrhalis.

Because fluoroquinolones, including FACTIVE, have been associated with serious adverse reactions (see WARNINGS) and for some patients ABECB is self-limiting, reserve FACTIVE for treatment of ABECB in patients who have no alternative treatment options.

Community-acquired pneumonia (of mild to moderate severity) caused by Streptococcus pneumoniae (including multi-drug resistant strains [MDRSP])*, Haemophilus influenzae, Moraxella catarrhalis, Mycoplasma pneumoniae, Chlamydia pneumoniae, or Klebsiella pneumoniae.

*MDRSP: multi-drug resistant Streptococcus pneumoniae, includes isolates previously known as PRSP (penicillin-resistant Streptococcus pneumoniae), and are strains resistant to two or more of the following antibiotics: penicillin (MIC ≥2 μg/mL), 2nd generation cephalosporins (e.g., cefuroxime), macrolides, tetracyclines and trimethoprim/sulfamethoxazole.

To reduce the development of drug-resistant bacteria and maintain the effectiveness of FACTIVE and other antibacterial drugs, FACTIVE should be used only to treat infections that are proven or strongly suspected to be caused by susceptible bacteria. When culture and susceptibility information are available, they should be considered in selecting or modifying antibacterial therapy. In the absence of such data, local epidemiology and susceptibility patterns may contribute to the empiric selection of therapy.

CONTRAINDICATIONS

FACTIVE is contraindicated in patients with a history of hypersensitivity to gemifloxacin, fluoroquinolone antibiotic agents, or any of the product components.

WARNINGS

Disabling and Potentially Irreversible Serious Adverse Reactions Including Tendinitis and Tendon Rupture, Peripheral Neuropathy, and Central Nervous System Effects:

Fluoroquinolones, including FACTIVE have been associated with disabling and potentially irreversible serious adverse reactions from different body systems that can occur together in the same patient. Commonly seen adverse reactions include tendinitis, tendon rupture, arthralgia, myalgia, peripheral neuropathy, and central nervous system effects (hallucinations, anxiety, depression, insomnia, severe headaches, and confusion). These reactions can occur within hours to weeks after starting FACTIVE. Patients of any age or without pre-existing risk factors have experienced these adverse reactions (See WARNINGS, Tendinitis and Tendon Rupture, Peripheral Neuropathy and Central Nervous System Effects).

Discontinue FACTIVE immediately at the first signs or symptoms of any serious adverse reaction. In addition, avoid the use of fluoroquinolones, including FACTIVE, in patients who have experienced any of these serious adverse reactions associated with fluoroquinolones.

Tendinitis and Tendon Rupture: Fluoroquinolones, including FACTIVE, have been associated with an increased risk of tendinitis and tendon rupture in all ages. This adverse reaction most frequently involves the Achilles tendon, and has also been reported with the rotator cuff (the shoulder), the hand, the biceps, the thumb, and other tendons. Tendinitis or tendon rupture can occur within hours or days after starting FACTIVE, or as long as several months after completion of therapy. Tendinitis and tendon rupture can occur bilaterally.
The risk of developing fluoroquinolone-associated tendinitis and tendon rupture is increased in patients over 60 years of age, in patients taking corticosteroid drugs, and in patients with kidney, heart or lung transplants. Other factors, in addition to age and corticosteroid use, that may independently increase the risk of tendon rupture include strenuous physical activity, renal failure, and previous tendon disorders such as rheumatoid arthritis. Tendinitis and tendon rupture have also occurred in patients taking fluoroquinolones who do not have the above risk factors. Discontinue FACTIVE if the patient experiences pain, swelling, inflammation or rupture of a tendon. Avoid fluoroquinolones, including FACTIVE, in patients who have a history of tendon disorders or have experienced tendinitis or tendon rupture. Patients should be advised to rest at the first sign of tendinitis or tendon rupture, and to contact their healthcare provider regarding changing to a non-quinolone antimicrobial drug.

Peripheral Neuropathy: Fluoroquinolones, including FACTIVE, have been associated with an increased risk of peripheral neuropathy. Cases of sensory or sensorimotor axonal polyneuropathy affecting small and/or large axons resulting in paresthesias, hypoesthesias, dysesthesias and weakness have been reported in patients receiving fluoroquinolones, including FACTIVE. Symptoms may occur soon after initiation of FACTIVE and may be irreversible in some patients. Discontinue FACTIVE immediately if the patient experiences symptoms of peripheral neuropathy, including pain, burning, tingling, numbness, and/or weakness or other alterations in sensations including light touch, pain, temperature, position sense, and vibratory sensation.

CNS Effects: Fluoroquinolones, including FACTIVE, have been associated with an increased risk of central nervous system (CNS) effects, including convulsions, increased intracranial pressure (including pseudotumor cerebri), and toxic psychosis. In clinical studies with FACTIVE, central nervous system (CNS) effects have been reported infrequently. As with other fluoroquinolones, FACTIVE should be used with caution in patients with CNS diseases such as epilepsy or patients predisposed to convulsions. CNS stimulation which may lead to tremors, restlessness, anxiety, lightheadedness, confusion, hallucinations, paranoia, depression, insomnia, and rarely suicidal thoughts or acts may also be caused by other fluoroquinolones. If these reactions occur in patients receiving FACTIVE, discontinue FACTIVE immediately and institute appropriate measures.

Exacerbation of Myasthenia Gravis: Fluoroquinolones, including FACTIVE, have neuromuscular blocking activity and may exacerbate muscle weakness in patients with myasthenia gravis. Postmarketing serious adverse reactions, including deaths and requirement for ventilatory support, have been associated with fluoroquinolone use in patients with myasthenia gravis. Avoid FACTIVE in patients with known history of myasthenia gravis. (See PRECAUTIONS/Information for Patients and Adverse Reactions/Post-Marketing Adverse Reactions.)

THE SAFETY AND EFFECTIVENESS OF FACTIVE IN CHILDREN, ADOLESCENTS (LESS THAN 18 YEARS OF AGE), PREGNANT WOMEN, AND LACTATING WOMEN HAVE NOT BEEN ESTABLISHED. (See PRECAUTIONS: Pediatric Use, Pregnancy and Nursing Mothers subsections.)

QT Effects: Fluoroquinolones may prolong the QT interval in some patients. FACTIVE should be avoided in patients with a history of prolongation of the QTc interval, patients with uncorrected electrolyte disorders (hypokalemia or hypomagnesemia), and patients receiving Class IA (e.g., quinidine, procainamide) or Class III (e.g., amiodarone, sotalol) antiarrhythmic agents.

Pharmacokinetic studies between gemifloxacin and drugs that prolong the QTc interval such as erythromycin, antipsychotics, and tricyclic antidepressants have not been performed. FACTIVE should be used with caution when given concurrently with these drugs, as well as in patients with ongoing proarrhythmic conditions, such as clinically significant bradycardia or acute myocardial ischemia. No cardiovascular morbidity or mortality attributable to QTc prolongation occurred with FACTIVE treatment in over 8119 patients, including 707 patients concurrently receiving drugs known to prolong the QTc interval and 7 patients with hypokalemia.

The likelihood of QTc prolongation may increase with increasing dose of the drug; therefore, the recommended dose should not be exceeded especially in patients with renal or hepatic impairment where the Cmax and AUC are slightly higher. QTc prolongation may lead to an increased risk for ventricular arrhythmias including torsades de pointes. The maximal change in the QTc interval occurs approximately 5-10 hours following oral administration of gemifloxacin.

Hypersensitivity Reactions: Serious hypersensitivity and/or anaphylactic reactions have been reported in patients receiving fluoroquinolone therapy, including FACTIVE. Hypersensitivity reactions reported in patients receiving fluoroquinolone therapy have occasionally been fatal. These reactions may occur following the first dose. Some reactions have been accompanied by cardiovascular collapse, hypotension/shock, seizure, loss of consciousness, tingling, angioedema (including tongue, laryngeal, throat or facial edema/swelling), airway obstruction (including bronchospasm, shortness of breath and acute respiratory distress), dyspnea, urticaria, itching and other serious skin reactions.

FACTIVE should be discontinued immediately at the appearance of any sign of an immediate type I hypersensitivity skin rash or any other manifestation of a hypersensitivity reaction; the need for continued fluoroquinolone therapy should be evaluated. As with other drugs, serious acute hypersensitivity reactions may require treatment with epinephrine and other resuscitative measures, including oxygen, intravenous fluids, antihistamines, corticosteroids, pressor amines and airway management as clinically indicated. (See PRECAUTIONS and ADVERSE REACTIONS.)

Other serious and sometimes fatal reqactions, some due to hypersensitivity and some due to uncertain etiology, have been reported rarely in patients receiving therapy with quinolones, including FACTIVE. These events may be severe and generally occur following the administration of multiple doses. Clinical manifestations may include one or more of the following:

- fever, rash or severe dermatologic reactions (e.g., toxic epidermal necrolysis, Stevens-Johnson Syndrome);
- vasculitis; arthralgia; myalgia; serum sickness;
- allergic pneumonitis;
- interstitial nephritis; acute renal insufficiency or failure;
- hepatitis; jaundice; acute hepatic necrosis or failure;
- anemia, including hemolytic and aplastic;
- thrombocytopenia, including thrombotic thrombocytopenic purpura; leukopenia agranulocytosis; pancytopenia; and/or other hematologic abnormalities.

Discontinue FACTIVE immediately at the first appearance of a skin rash, jaundice, or any other sign of hypersensitivity and institute supportive measures instituted (See PRECAUTIONS: Information for Patients and ADVERSE REACTIONS).

Clostridium difficile Associated Diarrhea: Clostridium difficile associated diarrhea (CDAD) has been reported with use of nearly all antibacterial agents, including FACTIVE, and may range in severity from mild diarrhea to fatal colitis. Treatment with antibacterial agents alters the normal flora of the colon leading to overgrowth of C. difficile.

C. difficile produces toxins A and B which contribute to the development of CDAD. Hypertoxin producing strains of C. difficile cause increased morbidity and mortality, as these infections can be refractory to antimicrobial therapy and may require colectomy. CDAD must be considered in all patients who present with diarrhea following antibiotic use. Careful medical history is necessary since CDAD has been reported to occur over two months after the administration of antibacterial agents.

If CDAD is suspected or confirmed, ongoing antibiotic use not directed against C. difficile may need to be discontinued. Appropriate fluid and electrolyte management, protein supplementation, antibiotic treatment of C. difficile, and surgical evaluation should be instituted as clinically indicated.

PRECAUTIONS

General: Prescribing FACTIVE in the absence of a proven or strongly suspected bacterial infection is unlikely to provide benefit to the patient and increases the risk of the development of drug-resistant bacteria.

Rash: In clinical studies, rash occurred more often with FACTIVE than with therapy with comparator agents (2.7% vs. 0.6%). Increasing incidence of rash was associated with younger age (especially below 40), female gender, use of hormone replacement therapy and longer durations of therapy (see Table 2). Urticarial reactions, some of which were not classified as rash, were more common in FACTIVE patients than in comparator patients (0.6% vs. 0.2%). FACTIVE should be discontinued in patients developing a rash or urticaria while on treatment. (See ADVERSE REACTIONS and CLINICAL STUDIES .)
Table 2. Rash Incidence in FACTIVE Treated Patients from the Clinical Studies Population* by Gender, Age, and Duration of Therapy

Gender & Age (yr) Category | Duration of FACTIVE Therapy
Gender & Age (yr) Category | 5 days | 7 days | 10 days** | 14 days**
Female < 40 | 10/399 (2.5%) | 49/407 (12.0%) | 20/131 (15.3%) | 7/31 (22.6%)
Female ≥ 40 | 30/1438 (2.1%) | 34/887 (3.8%) | 19/308 (6.2%) | 10/126 (7.9%)
Male < 40 | 6/356 (1.7%) | 26/453 (5.7%) | 7/74 (9.5%) | 3/39 (7.7%)
Male ≥ 40 | 10/1503 (0.7%) | 26/984 (2.6%) | 9/345 (2.6%) | 3/116 (2.6%)
Totals | 56/3696 (1.5%) | 135/2732 (4.9%) | 55/858 (6.4%) | 23/312 (7.4%)

*includes patients from studies of community-acquired pneumonia, acute bacterial exacerbation of chronic bronchitis, and other indications
**exceeds the recommended duration of therapy (see DOSAGE AND ADMINISTRATION)

The most common form of rash associated with FACTIVE was described as maculopapular and mild to moderate in severity. Eighty percent of rashes resolved within 14 days. Approximately 10% of the rashes (0.5% of all patients) were described as of severe intensity and approximately 10% of those with rash were treated with systemic steroids. There were no documented cases in the clinical trials of more serious skin reactions known to be associated with significant morbidity or mortality.

Moderate to severe photosensitivity/phototoxicity reactions, the latter of which may manifest as exaggerated sunburn reactions (e.g., burning, erythema, exudation, vesicles, blistering, edema) involving areas exposed to light (typically the face, “V” area of the neck, extensor surfaces of the forearms, dorsa of the hands), can be associated with use of quinolones after sun or UV light exposure. Therefore excessive exposure to these sources of light should be avoided. Drug therapy should be discontinued if phototoxicity occurs. (See ADVERSE REACTIONS and ADVERSE REACTIONS/ Post-Marketing Adverse Reactions.)

Hepatic Effects: Liver enzyme elevations (increased ALT and/or AST) occurred at similar rates in patients receiving FACTIVE 320 mg daily relative to comparator antimicrobial agents (ciprofloxacin, levofloxacin, clarithromycin/cefuroxime axetil, amoxicillin/clavulanate potassium, and ofloxacin). In patients who received gemifloxacin at doses of 480 mg per day or greater there was an increased incidence of elevations in liver enzymes. (See ADVERSE REACTIONS.)

There were no clinical symptoms associated with these liver enzyme elevations. The liver enzyme elevations resolved following cessation of therapy. The recommended dose of FACTIVE 320 mg daily should not be exceeded and the recommended length of therapy should not be exceeded. (See DOSAGE AND ADMINISTRATION.)

Renal Effects: Alteration of the dosage regimen is necessary for patients with impairment of renal function (creatinine clearance ≤40 mL/min). (See DOSAGE AND ADMINISTRATION.)

Adequate hydration of patients receiving FACTIVE should be maintained to prevent the formation of a highly concentrated urine.

Information for Patients

Advise the patient to read the FDA-approved patient labeling (Medication Guide)

Serious Adverse Reactions

Advise patients to stop taking FACTIVE if they experience an adverse reaction and to call their healthcare provider for advice on completing the full course of treatment with another antibacterial drug.

Inform patients of the following serious adverse reactions that have been associated with FACTIVE or other fluoroquinolone use:

- Disabling and potentially irreversible serious adverse reactions that may occur together, including tendinitis and tendon rupture, peripheral neuropathies, and central nervous system effects, have been associated with use of FACTIVE and may occur together in the same patient. Inform patients to stop taking FACTIVE immediately if they experience an adverse reaction and to call their healthcare provider;
- Tendinitis and tendon rupture: instruct patients to contact their healthcare provider if they experience pain, swelling, or inflammation of a tendon, or weakness or inability to use one of their joints; rest and refrain from exercise; and discontinue FACTIVE treatment. The risk of severe tendon disorders with fluoroquinolones is higher in older patients usually over 60 years of age, in patients taking corticosteroid drugs, and in patients with kidney, heart or lung transplants;
- Peripheral neuropathies: Inform patients that peripheral neuropathies have been associated with the use of FACTIVE, that symptoms may occur soon after initiation of therapy and may be irreversible. If symptoms of peripheral neuropathy including pain, burning, tingling, numbness and/or weakness develop, patients should immediately discontinue FACTIVE and contact their physician;
- Central nervous system effects (for example, convulsions, dizziness, lightheadedness, increased intracranial pressure): Inform patients that convulsions have been reported in patients receiving fluoroquinolones, including FACTIVE. Patients should notify their physician before taking FACTIVE if they have a history of convulsions, seizures, or epilepsy; Inform patients that other central nervous system problems such as tremors, restlessness, lightheadedness, confusion and hallucinations may occur rarely;
- Exacerbation of Myasthenia Gravis: Inform patients that fluoroquinolones like FACTIVE may cause worsening of myasthenia gravis symptoms, including muscle weakness and breathing problems. Patients should call their healthcare provider right away if they have any worsening muscle weakness or breathing problems;
- Hypersensitivity Reactions: Inform patients that FACTIVEmay be associated with hypersensitivity reactions, including anaphylactic reactions, even following a single dose; patients should immediately discontinue the drug at the sign of a rash or other allergic reaction and seek medical care; Inform patients that FACTIVE has been associated with rash and hives. Rash occurs more commonly in those under 40, especially women and in women on hormone replacement therapy. The incidence of rash increases with duration more than 5 days and particularly longer than 7 days. Patients should discontinue FACTIVE and call their healthcare provider if they develop a rash;
- Diarrhea: Inform patients that diarrhea is a common problem caused by antibiotics which usually ends when the antibiotic is discontinued. Sometimes after starting treatment with antibiotics, patients can develop watery and bloody stools (with or without stomach cramps and fever) even as late as two or more months after having taken the last dose of the antibiotic. If this occurs, patients should contact their physician as soon as possible;
- Prolongation of the QT interval: inform patients of the following:that FACTIVE may cause changes in the electrocardiogram (QTc interval prolongation);
  - that FACTIVE may cause changes in the electrocardiogram (QTc interval prolongation);
  - that FACTIVE should be avoided in patients receiving Class IA (e.g., quinidine, procainamide) or Class III (e.g., amiodarone, sotalol) antiarrhythmic agents;
  - that FACTIVE should be used with caution in patients receiving drugs that affect the QTc interval such as cisapride, erythromycin, antipsychotics, and tricyclic antidepressants;
  - to inform their physician of any personal or family history of QTc prolongation or proarrhythmic conditions such as hypokalemia, bradycardia, or recent myocardial ischemia;
  - to contact their physician if they experience palpitations or fainting spells while taking FACTIVE;
- that FACTIVE may cause dizziness; if this occurs, patients should not operate an automobile or machinery or engage in activities requiring mental alertness or coordination;
- Photosensitivity/Phototoxicity: Inform patients that photosensitivity/phototoxicity has been reported in patients receiving quinolones. Patients should minimize or avoid exposure to natural or artificial sunlight (tanning beds or UVA/B treatment) while taking quinolones. If patients need to be outdoors while using quinolones, they should wear loose-fitting clothes that protect skin from sun exposure and discuss other sun protection measures with their physician. If a sunburn-like reaction or skin eruption occurs, patients should contact their physician; (See CLINICAL PHARMACOLOGY: Photosensitivity Potential).

Other Information
Advise Patients:

- that increases of the International Normalized Ratio (INR), or prothrombin time (PT), and/or clinical episodes of bleeding have been noted with concurrent administration of warfarin or its derivatives, and FACTIVE. Patients should notify their physicians if they are taking warfarin or its derivatives;
- to inform their physician of any other medications when taken concurrently with FACTIVE, including over-the-counter medications and dietary supplements;
- that FACTIVE may be taken with or without meals;
- to drink fluids liberally;
- not to take antacids containing magnesium and/or aluminum or products containing ferrous sulfate (iron), multivitamin preparations containing zinc or other metal cations, or Videx (didanosine) chewable/buffered tablets or the pediatric powder for oral solution within 3 hours before or 2 hours after taking FACTIVE tablets;
- that FACTIVE should be taken at least 2 hours before sucralfate;
- that antibacterial drugs including FACTIVE should only be used to treat bacterial infections. They do not treat viral infections (e.g., the common cold). When FACTIVE is prescribed to treat a bacterial infection, patients should be told that although it is common to feel better early in the course of therapy, the medication should be taken exactly as directed. Skipping doses or not completing the full course of therapy may (1) decrease effectiveness of the immediate treatment and (2) increase the likelihood that bacteria will develop resistance and will not be treatable by FACTIVE or other antibacterial drugs in the future.

Drug Interactions: Administration of repeat doses of FACTIVE had no effect on the repeat dose pharmacokinetics of theophylline, digoxin or an ethinylestradiol/levonorgestrol oral contraceptive product in healthy subjects. (See CLINICAL PHARMACOLOGY: Drug-Drug Interactions.)

Concomitant administration of FACTIVE and calcium carbonate, cimetidine, omeprazole, or an estrogen/progesterone oral contraceptive produced minor changes in the pharmacokinetics of gemifloxacin, which were considered to be without clinical significance. (See CLINICAL PHARMACOLOGY.)

Concomitant administration of FACTIVE with probenecid resulted in a 45% increase in systemic exposure to gemifloxacin. (See CLINICAL PHARMACOLOGY .)

FACTIVE had no significant effect on the anticoagulant effect of warfarin in healthy subjects on stable warfarin therapy. However, post-marketing reports of increases in the INR, or PT, and/or clinical episodes of bleeding in patients have been noted with the use of quinolones, including FACTIVE, and warfarin, or its derivatives. In addition, infectious disease and its accompanying inflammatory process, age and general status of the patient are risk factors for increased anticoagulation activity. Therefore, the PT, INR or other suitable coagulation test should be closely monitored if a quinolone antimicrobial, including FACTIVE, is administered concomitantly with warfarin or its derivatives.

Quinolones form chelates with alkaline earth and transition metals. The absorption of oral gemifloxacin is significantly reduced by the concomitant administration of an antacid containing aluminum and magnesium. Magnesium- and/or aluminum-containing antacids, products containing ferrous sulfate (iron), multivitamin preparations containing zinc or other metal cations, or Videx® (didanosine) chewable/buffered tablets or the pediatric powder for oral solution should not be taken within 3 hours before or 2 hours after FACTIVE. Sucralfate should not be taken within 2 hours of FACTIVE. (See CLINICAL PHARMACOLOGY.)

Carcinogenesis, Mutagenesis, Impairment of Fertility
Carcinogenesis: Long term studies in animals to determine the carcinogenic potential of gemifloxacin have not been conducted.

Photocarcinogenesis: Gemifloxacin did not shorten the time to development of UVR-induced skin tumors in hairless albino (Skh-1) mice; thus, it was not photocarcinogenic in this model. These mice received oral gemifloxacin and concurrent irradiation with simulated sunlight 5 days per week for 40 weeks followed by a 12-week treatment-free observation period. The daily dose of UV radiation used in this study was approximately 1/3 of the minimal dose of UV radiation that would induce erythema in Caucasian humans. The median time to the development of skin tumors in the hairless mice was similar in the vehicle control group (36 weeks) and those given up to 100 mg/kg gemifloxacin daily (39 weeks). Following repeat doses of 100 mg/kg gemifloxacin per day, the mice had skin gemifloxacin concentrations of approximately 7.4 μg/g. Plasma levels following this dose were approximately 1.4 μg/mL in the mice around the time of irradiation. There are no data on gemifloxacin skin levels in humans, but the mouse plasma gemifloxacin levels are in the expected range of human plasma Cmax levels (0.7-2.6 μg/mL, with an overall mean of about 1.6 μg/mL) following multiple 320 mg oral doses.

Mutagenesis: Gemifloxacin was not mutagenic in 4 bacterial strains (TA 98, TA 100, TA 1535, TA 1537) used in an Ames Salmonella reversion assay. It did not induce micronuclei in the bone marrow of mice following intraperitoneal doses of up to 40 mg/kg and it did not induce unscheduled DNA synthesis in hepatocytes from rats which received oral doses of up to 1600 mg/kg. Gemifloxacin was clastogenic in vitro in the mouse lymphoma and human lymphocyte chromosome aberration assays. It was clastogenic in vivo in the rat micronucleus assay at oral and intravenous dose levels (≥800 mg/kg and ≥40 mg/kg, respectively) that produced bone marrow toxicity. Fluoroquinolone clastogenicity is apparently due to inhibition of mammalian topoisomerase activity which has threshold implications.

Impairment of Fertility: Gemifloxacin did not affect the fertility of male or female rats at AUC levels following oral administration (216 and 600 mg/kg/day) that were approximately 3- to 4-fold higher than the AUC levels at the clinically recommended dose.

Pregnancy: Teratogenic Effects. Pregnancy Category C. Gemifloxacin treatment during organogenesis caused fetal growth retardation in mice (oral dosing at 450 mg/kg/day), rats (oral dosing at 600 mg/kg/day) and rabbits (IV dosing at 40 mg/kg/day) at AUC levels which were 2-, 4- and 3-fold those in women given oral doses of 320 mg. In rats, this growth retardation appeared to be reversible in a pre- and postnatal development study (mice and rabbits were not studied for the reversibility of this effect). Treatment of pregnant rats at 8-fold clinical exposure (based upon AUC comparisons) caused fetal brain and ocular malformations in the presence of maternal toxicity. The overall no-effect exposure level in pregnant animals was approximately 0.8 to 3-fold clinical exposure.

The safety of FACTIVE in pregnant women has not been established. FACTIVE should not be used in pregnant women unless the potential benefit to the mother outweighs the risk to the fetus. There are no adequate and well-controlled studies in pregnant women.

Nursing Mothers: Gemifloxacin is excreted in the breast milk of rats. There is no information on excretion of gemifloxacin into human milk. Therefore, FACTIVE should not be used in lactating women unless the potential benefit to the mother outweighs the risk.

Pediatric Use: Safety and effectiveness in children and adolescents less than 18 years of age have not been established. Fluoroquinolones, including gemifloxacin, cause arthropathy and osteochondrosis in immature animals. (See WARNINGS.)

Geriatric Use: Geriatric patients are at increased risk for developing severe tendon disorders including tendon rupture when being treated with a fluoroquinolone such as FACTIVE. This risk is further increased in patients receiving concomitant corticosteroid therapy. Tendinitis or tendon rupture can involve the Achilles, hand, shoulder, or other tendon sites and can occur during or after completion of therapy; cases occurring up to several months after fluoroquinolone treatment have been reported. Caution should be used when prescribing FACTIVE to elderly patients especially those on corticosteroids. Patients should be informed of this potential side effect and advised to discontinue FACTIVE and contact their healthcare provider if any symptoms of tendinitis or tendon rupture occur (See Boxed Warning, WARNINGS, and ADVERSE REACTIONS/Post-Marketing Adverse Event Reports.)

Of the total number of subjects in clinical studies of FACTIVE, 29% (2314) were 65 and over, while 11% (865) were 75 and over. No overall difference in effectiveness was observed between these subjects and younger subjects; the adverse event rate for this group was similar to or lower than that for younger subjects with the exception that the incidence of rash was lower in geriatric patients compared to patients less than 40 years of age.

Elderly patients may be more susceptible to drug-associated effects on the QT interval. Therefore, FACTIVE should be avoided in patients taking drugs that can result in prolongation of the QT interval (e.g., Class IA or Class III antiarrhythmics) or in patients with risk factors for torsades de pointes (e.g., known QT prolongation, uncorrected hypokalemia).

ADVERSE REACTIONS

In clinical studies, 8119 patients received daily oral doses of 320 mg FACTIVE. In addition, 1797 healthy volunteers and 81 patients with renal or hepatic impairment received single or repeat doses of gemifloxacin in clinical pharmacology studies. The majority of adverse reactions experienced by patients in clinical trials were considered to be of mild to moderate severity.

FACTIVE was discontinued because of an adverse event (determined by the investigator to be possibly or probably related to drug) in 2.0% of patients, primarily due to rash (0.8%), nausea (0.3%), diarrhea (0.3%), urticaria (0.2%) and vomiting (0.2%). Comparator antibiotics were discontinued because of an adverse event at an overall comparable rate of 2.1%, primarily due to diarrhea (0.5%), nausea (0.4%), vomiting (0.3%), rash (0.3%), abdominal pain (0.2%) and vertigo (0.2%).

The most commonly reported adverse events with a frequency of ≥2% for patients receiving 320 mg FACTIVE versus comparator drug (beta-lactam antibiotics, macrolides or other fluoroquinolones) are as follows: diarrhea 5.0% vs. 6.2%; rash 3.5% vs. 1.1%; nausea 3.7% vs. 4.5%; headache 4.2% vs. 5.2%; abdominal pain 2.2% vs. 2.2%; vomiting 1.6% vs. 2.0%; and dizziness 1.7% vs. 2.6%.

Adverse Events with a Frequency of Less than 1%

Additional drug-related adverse events (possibly or probably related) in the 8119 patients, with a frequency of >0.1% to ≤1% included: abdominal pain, anorexia, constipation, dermatitis, dizziness, dry mouth, dyspepsia, fatigue, flatulence, fungal infection, gastritis, genital moniliasis, genital pruritus, hyperglycemia, increased alkaline phosphatase, increased ALT, increased AST, increased creatine phosphokinase, insomnia, leukopenia, pruritus, somnolence, taste perversion, thrombocythemia, urticaria, vaginitis, and vomiting.

Other adverse events reported from clinical trials which have potential clinical significance and which were considered to have a suspected relationship to the drug, that occurred in ≤0.1% of patients were: abnormal urine, abnormal vision, anemia, arthralgia, asthenia, back pain, bilirubinemia, dyspnea, eczema, eosinophilia, facial edema, flushing, gastroenteritis, granulocytopenia, hot flashes, increased GGT, increased non-protein nitrogen, leg cramps, moniliasis, myalgia, nervousness, non-specified gastrointestinal disorder, pain, pharyngitis, photosensitivity/phototoxicity reactions, pneumonia, thrombocytopenia, tremor, vertigo. (See PRECAUTIONS.)

In clinical trials of acute bacterial exacerbation of chronic bronchitis (ABECB) and community acquired pneumonia (CAP), the incidences of rash were as follows (Table 3):
Table 3. Incidence of Rash by Clinical Indication in Patients Treated with FACTIVE

 | ABECB (5 days) N = 2284 |  | CAP (5 days) N = 256 |  | CAP (7 days) N = 643
 | n/N | % | n/N | % | n/N | %
Totals | 27/2284 | 1.2 | 1/256 | 0.4 | 26/643 | 4.0
Females, < 40 years | NA* |  | 1/37 | 2.7 | 8/88 | 9.1
Females, ≥ 40 years | 16/1040 | 1.5 | 0/73 | 0 | 5/214 | 2.3
Males, < 40 years | NA* |  | 0/65 | 0 | 5/101 | 5.0
Males, ≥ 40 years | 11/1203 | 0.9 | 0/81 | 0 | 8/240 | 3.3

* insufficient number of patients in this category for a meaningful analysis

(See PRECAUTIONS).

Laboratory Changes: The percentages of patients who received multiple doses of FACTIVE and had a laboratory abnormality are listed below. It is not known whether these abnormalities were related to FACTIVE or an underlying condition.

Clinical Chemistry: increased ALT (1.7%), increased AST (1.3%), increased creatine phosphokinase (0.7%), increased alkaline phosphatase (0.4%), increased total bilirubin (0.4%), increased potassium (0.3%), decreased sodium (0.2%), increased blood urea nitrogen (0.3%), decreased albumin (0.3%), increased serum creatinine (0.2%), decreased calcium (0.1%), decreased total protein (0.1%), decreased potassium (0.1%), increased sodium (0.1%), increased lactate dehydrogenase (<0.1%) and increased calcium (<0.1%).

CPK elevations were noted infrequently: 0.7% in FACTIVE patients vs. 0.7% in the comparator patients.

Hematology: increased platelets (1.0%), decreased neutrophils (0.5%), increased neutrophils (0.5%), decreased hematocrit (0.3%), decreased hemoglobin (0.2%), decreased platelets (0.2%), decreased red blood cells (0.1%), increased hematocrit (0.1%), increased hemoglobin (0.1%), and increased red blood cells (0.1%).

In clinical studies, approximately 7% of the FACTIVE treated patients had elevated ALT values immediately prior to entry into the study. Of these patients, approximately 15% showed a further elevation of their ALT at the on-therapy visit and 9% showed a further elevation at the end of therapy visit. None of these patients demonstrated evidence of hepatocellular jaundice. For the pooled comparators, approximately 6% of patients had elevated ALT values immediately prior to entry into the study. Of these patients, approximately 7% showed a further elevation of their ALT at the on-therapy visit and 4% showed a further elevation at the end of therapy visit.

In a clinical trial where 638 patients received either a single 640 mg dose of gemifloxacin or 250 mg BID of ciprofloxacin for 3 days, there was an increased incidence of ALT elevations in the gemifloxacin arm (3.9%) vs. the comparator arm (1.0%). In this study, two patients experienced ALT elevations of 8 to 10 times the upper limit of normal. These elevations were asymptomatic and reversible.

Post-Marketing Adverse Reactions: The majority of the post-marketing adverse events reported were cutaneous and most of these were rash. Some of these cutaneous adverse events were considered serious. The majority of the rashes occurred in women and in patients under 40 years of age.

The following are additional adverse reactions reported during the post-marketing use of FACTIVE. Since these reactions are reported voluntarily from a population of uncertain size, it is impossible to reliably estimate their frequency or establish a causal relationship to FACTIVE exposure:

- peripheral neuropathy that may be irreversible;
- anaphylactic reaction, erythema multiforme, skin exfoliation, facial swelling;
- exacerbation of myasthenia gravis;
- hemorrhage, increased international normalized ratio (INR), retinal hemorrhage;
- peripheral edema;
- renal failure;
- prolonged QT, supraventricular tachycardia, syncope, transient ischemic attack;
- photosensitivity/phototoxicity reaction (See PRECAUTIONS.);
- antibiotic-associated colitis;
- tendon rupture.

OVERDOSAGE

Any signs or symptoms of overdosage should be treated symptomatically. No specific antidote is known. In the event of acute oral overdosage, the stomach should be emptied by inducing vomiting or by gastric lavage; the patient should be carefully observed and treated symptomatically with appropriate hydration maintained. Hemodialysis removes approximately 20 to 30% of an oral dose of gemifloxacin from plasma.

Mortality occurred at oral gemifloxacin doses of 1600 mg/kg in rats and 320 mg/kg in mice. The minimum lethal intravenous doses in these species were 160 and 80 mg/kg, respectively. Toxic signs after administration of a single high oral dose (400 mg/kg) of gemifloxacin to rodents included ataxia, lethargy, piloerection, tremor, and clonic convulsions.

DOSAGE AND ADMINISTRATION

FACTIVE can be taken with or without food and should be swallowed whole with a liberal amount of liquid. The recommended dose of FACTIVE is 320 mg daily, according to the following table (Table 4).
Table 4. Recommended Dosage Regimen of FACTIVE

The clinical decision regarding the use of a 5 or 7 day regimen should be guided by results of the initial sputum culture.

INDICATION | DOSE / DURATION
Acute bacterial exacerbation of chronic bronchitis | One 320 mg tablet daily for 5 days
Community-acquired pneumonia (of mild to moderate severity)
due to known or suspected S. pneumoniae, H. influenzae, M. pneumoniae, or C. pneumoniae infection | One 320 mg tablet daily for 5 days
due to known or suspected MDRSP*, K. pneumoniae, or M. catarrhalis infection | One 320 mg tablet daily for 7 days

*MDRSP: multi-drug resistant Streptococcus pneumoniae, includes isolates previously known as PRSP (penicillin-resistant Streptococcus pneumoniae), and are strains resistant to two or more of the following antibiotics: penicillin (MIC 2 µg/mL), 2nd generation cephalosporins (e.g., cefuroxime), macrolides, tetracyclines and trimethoprim/sulfamethoxazole.

The recommended dose and duration of FACTIVE should not be exceeded (see Table 2).

Use in Renally Impaired Patients: Dose adjustment in patients with creatinine clearance >40 mL/min is not required. Modification of the dosage is recommended for patients with creatinine clearance 40 mL/min. Table 5 provides dosage guidelines for use in patients with renal impairment.
Table 5. Recommended Doses for Patients with Renal Impairment

Creatinine Clearance; (mL/min) | Dose
>40 | See Usual Dosage
40 | 160 mg every 24 hours

Patients requiring routine hemodialysis or continuous ambulatory peritoneal dialysis (CAPD) should receive 160 mg every 24 hours.

When only the serum creatinine concentration is known, the following formula may be used to estimate creatinine clearance.

Creatinine Clearance Formula

Women: 0.85 x the value calculated for men

Use in Hepatically Impaired Patients: No dosage adjustment is recommended in patients with mild (Child-Pugh Class A), moderate (Child-Pugh Class B) or severe (Child-Pugh Class C) hepatic impairment.

Use in Elderly: No dosage adjustment is recommended.

HOW SUPPLIED

FACTIVE (gemifloxacin mesylate) is available as white to off-white, oval, film-coated tablets with breaklines and GE 320 debossed on both faces. Each tablet contains gemifloxacin mesylate equivalent to 320 mg of gemifloxacin.

320 mg Unit of Use (CR*) 5's NDC 44001-321-05
320 mg Unit of Use (CR*) 7's NDC 44001-321-07

*Child Resistant

Storage

Store at 25ºC (77ºF); excursions permitted to 15º-30ºC (59º-86ºF) [see USP Controlled Room Temperature]. Protect from light.

ANIMAL PHARMACOLOGY

Quinolones have been shown to cause arthropathy in immature animals. Degeneration of articular cartilage occurred in juvenile dogs given at least 192 mg/kg/day gemifloxacin in a 28-day study (producing about 6 times the systemic exposure at the clinical dose), but not in mature dogs. There was no damage to the articular surfaces of joints in immature rats given repeated doses of up to 800 mg/kg/day.

Some quinolones have been reported to have proconvulsant properties that are potentiated by the concomitant administration of non-steroidal anti-inflammatory drugs (NSAIDs). Gemifloxacin alone had effects in tests of behavior or CNS interaction typically at doses of at least 160 mg/kg. No convulsions occurred in mice given the active metabolite of the NSAID, fenbufen, followed by 80 mg/kg gemifloxacin.

Dogs given 192 mg/kg/day (about 6 times the systemic exposure at the clinical dose) for 28 days, or 24 mg/kg/day (approximately equivalent to the systemic exposure at the clinical dose) for 13 weeks showed reversible increases in plasma ALT activities and local periportal liver changes associated with blockage of small bile ducts by crystals containing gemifloxacin.

Quinolones have been associated with prolongation of the electrocardiographic QT interval in dogs. Gemifloxacin produced no effect on the QT interval in dogs dosed orally to provide about 4 times human therapeutic plasma concentrations at Cmax, and transient prolongation after intravenous administration at more than 4 times human plasma levels at Cmax. Gemifloxacin exhibited weak activity in the cardiac IKr (hERG) channel inhibition assay, having an IC50 of approximately 270 μM.

Gemifloxacin, like many other quinolones, tends to crystallize at the alkaline pH of rodent urine, resulting in a nephropathy in rats that is reversible on drug withdrawal (oral no-effect dose 24 mg/kg/day).

Gemifloxacin was weakly phototoxic to hairless mice given a single 200 mg/kg oral dose and exposed to UVA radiation. However, no evidence of phototoxicity was observed at 100 mg/kg/day dosed orally for 13 weeks in a standard hairless mouse model, using simulated sunlight.

CLINICAL STUDIES

Acute Bacterial Exacerbation of Chronic Bronchitis (ABECB)

FACTIVE (320 mg once daily for 5 days) was evaluated for the treatment of acute bacterial exacerbation of chronic bronchitis in three pivotal double-blind, randomized, actively-controlled clinical trials (studies 068, 070, and 212). The primary efficacy parameter in these studies was the clinical response at follow-up (day 13 to 24). The results of the clinical response at follow-up for the principal ABECB studies demonstrate that FACTIVE 320 mg PO once daily for 5 days was at least as good as the comparators given for 7 days. The results are shown in Table 6 below.
Table 6. Clinical Response at Follow-Up (Test of Cure): Pivotal ABECB Studies

Drug Regimen | Success Rate % (n/N) | Treatment Difference (95% CI)
Study 068
FACTIVE 320 mg x 5 days | 86.0 (239/278) | 1.2 (-4.7, 7.0)
Clarithromycin 500 mg BID x 7 days | 84.8 (240/283) | 1.2 (-4.7, 7.0)
Study 070
FACTIVE 320 mg x 5 days | 93.6 (247/264) | 0.4 (-3.9, 4.6)
Amoxicillin/clavulanate 500 mg/125 mg TID x 7 days | 93.2 (248/266) | 0.4 (-3.9, 4.6)
Study 212
FACTIVE 320 mg x 5 days | 88.2 (134/152) | 3.1 (-4.7, 10.7)
Levofloxacin 500 mg x 7 days | 85.1 (126/148) | 3.1 (-4.7, 10.7)

Community Acquired Pneumonia (CAP)

5 Day Treatment Regimen

To evaluate the safety and efficacy of a 5-day course of FACTIVE, 510 outpatient and hospitalized adults with clinically and radiologically determined mild to moderate community-acquired pneumonia were clinically evaluated in a double-blind, randomized, prospective, multicenter study comparing FACTIVE 320 mg for five days to FACTIVE 320 mg for seven days (Study OP-634-001).

Clinical success rates in the clinically evaluable population were 95.0% in the 5 day group and 92.1% in the 7 day group.
Table 7. Clinical Response at Follow-Up (Test of Cure): Study OP-634-001

Drug Regimen | Success Rate % (n/N) | Treatment Difference (95% CI)
Study OP-634-001
FACTIVE 320 mg x 5 days | 95.0 (230/242) | 3.0 (-1.5, 7.4)
FACTIVE 320 mg x 7 days | 92.1 (209/227) | 3.0 (-1.5, 7.4)

The microbiological efficacy of the 5-day regimen was documented for pathogens listed in Table 8 below.
Table 8. Bacterial Eradication by Pathogen for Patients Treated with FACTIVE in Study OP-634-001

 | 5-day |  | 7-day
Pathogen | n/N | % | n/N | %
Streptococcus pneumoniae | 26/26 | 100 | 34/40 | 85.0
Mycoplasma pneumoniae | 22/25 | 88.0 | 19/20 | 95.0
Haemophilus influenzae | 21/22 | 95.5 | 18/18 | 100
Chlamydia pneumoniae | 17/18 | 94.4 | 30/31 | 96.8

7 Day Treatment Regimen

Previous clinical studies evaluated the efficacy of FACTIVE in a 7-day treatment of CAP in adults. This clinical program consisted of three double-blind, randomized, actively-controlled clinical studies (studies 011, 012, and 049) and one open-label, actively-controlled study (study 185). In addition, two uncontrolled studies (studies 061 and 287) were conducted. Three of the studies, controlled study 011 and the uncontrolled studies, had a fixed 7-day duration of treatment for FACTIVE. Controlled study 011 compared a 7-day course of FACTIVE with a 10-day treatment course of amoxicillin/clavulanate (1g/125 mg TID) and clinical success rates were similar between treatment arms. The results of comparative studies 049, 185, and 012 were supportive although treatment duration could have been 7 to 14 days. The results of the clinical studies with a fixed 7-day duration of FACTIVE are shown in Table 9.

Table 9. Clinical Response at Follow-Up (Test of Cure): CAP Studies with a Fixed 7-day Duration of Treatment

Drug Regimen | Success Rate % (n/N) | Treatment Difference (95% CI)*
Study 011
FACTIVE 320 mg x 7 days | 88.7 (102/115) | 1.1 (-7.3, 9.5)
Amoxicillin/clavulanate 1 g/125 mg TID x 10 days | 87.6 (99/113) | 1.1 (-7.3, 9.5)
Study 061
FACTIVE 320 mg x 7 days | 91.7 (154/168) | (86.1, 95.2)
Study 287
FACTIVE 320 mg x 7 days | 89.8 (132/147) | (84.9, 94.7)

*For uncontrolled studies, the 95% CI around the success rate is shown

The combined bacterial eradication rates for patients treated with a fixed 7-day treatment regimen of FACTIVE are shown in Table 10.
Table 10. Bacterial Eradication by Pathogen for Patients Treated with FACTIVE in Studies with a Fixed 7-day Duration of Treatment

Pathogen | n/N | %
S. pneumoniae | 102/117 | 87.2
M. pneumoniae | 40/42 | 95.2
H. influenzae | 48/53 | 90.6
C. pneumoniae | 43/45 | 95.6
K. pneumoniae | 18/20 | 90.0
M. catarrhalis | 11/12 | 91.7

7 Day Treatment Regimen of Community-Acquired Pneumonia Due to Multi-Drug Resistant Streptococcus pneumoniae (MDRSP)

FACTIVE was also effective in the treatment of CAP due to multi-drug resistant Streptococcus pneumoniae (MDRSP*). Of 35 patients with MDRSP treated for 7 days, 29 (82.9%) achieved clinical and bacteriological success at follow-up. The clinical and bacteriological success for the 35 patients with MDRSP isolates are shown in Table 11.

*MDRSP: multi-drug resistant Streptococcus pneumoniae, includes isolates previously known as PRSP (penicillin-resistant Streptococcus pneumoniae), and are strains resistant to two or more of the following antibiotics: penicillin (MIC ≥2 μg/mL), 2nd generation cephalosporins (e.g., cefuroxime), macrolides, tetracyclines and trimethoprim/sulfamethoxazole.
Table 11. Clinical and Bacteriological Success for 35 Patients Treated with FACTIVE in CAP Studies with a 7-day Duration of Treatment for MDRSP

Screening Susceptibility | Clinical Success |  | Bacteriological Success
Screening Susceptibility | n/Na | % | n/Nb | %
Penicillin-resistant | 15/16 | 93.8 | 15/16 | 93.8
2nd generation cephalosporin-resistant | 20/22 | 90.9 | 20/22 | 90.9
Macrolide-resistantc | 24/28 | 85.7 | 23/28 | 82.1
Trimethoprim/sulfamethoxazole-resistant | 23/26 | 88.5 | 23/26 | 88.5
Tetracycline-resistant | 21/27 | 77.8 | 20/27 | 74.1

an = the number of patients successfully treated; N = number of patients with MDRSP
bn = the number of bacteriological isolates successfully treated; N = number of isolates studied
cMacrolide antibiotics tested include clarithromycin and erythromycin

Not all isolates were resistant to all antimicrobial classes tested. Success and eradication rates are summarized in Table 12 below.
Table 12. Resistant Streptococcus pneumoniae Clinical Success and Bacteriological Eradication Rates

S. pneumoniae with MDRSP | Clinical Cure Rate |  | Bacteriological Eradication Rate
 | n/N | % | n/N | %
Resistant to 2 antimicrobials | 8/11 | 72.7 | 7/11 | 63.6
Resistant to 3 antimicrobials | 5/7 | 71.4 | 5/7 | 71.4
Resistant to 4 antimicrobials | 8/9 | 88.9 | 8/9 | 88.9
Resistant to 5 antimicrobials | 8/8 | 100 | 8/8 | 100
Bacteremia with MDRSP | 3/3 | 100 | 3/3 | 100

Clinical Safety Study of Rash

To further characterize gemifloxacin-associated rash, which in early clinical studies appeared to be associated with age less than 40 and female gender, a clinical pharmacology study was conducted. The study enrolled 1,011 healthy female volunteers less than 40 years of age. Subjects were randomized in a 5:1 ratio to receive either FACTIVE 320 mg PO daily (819 subjects) or ciprofloxacin 500 mg PO twice daily for 10 days (164 subjects). This study was designed to enroll subjects at a high risk for rash (women <40 years of age and dosing beyond the recommended duration of therapy for FACTIVE [10 days]) and over estimates the risk to patients taking FACTIVE as prescribed. Subjects who received FACTIVE were 7 times more likely to develop rash than those who received ciprofloxacin. Of the 260 rashes in subjects receiving FACTIVE, the majority of rashes were maculopapular and of mild to moderate severity; 7% of the rashes were reported as severe, and severity appeared to correlate with the extent of the rash. In 68% of the subjects reporting a severe rash and approximately 25% of all those reporting rash, >60% of the body surface area was involved; the characteristics of the rash were otherwise indistinguishable from those subjects reporting a mild rash. The histopathology was consistent with the clinical observation of uncomplicated exanthematous morbilliform eruption. Approximately 11% of the rashes were described as being “urticaria-like”. There were no documented cases of hypersensitivity syndrome or findings suggestive of angioedema or other serious cutaneous reactions.

The majority of rashes (81.9%) occurred on days 8 through 10 of the planned 10 day course of FACTIVE; 2.7% of rash events occurred within one day of the start of dosing. The median duration of rash was 6 days. The rash resolved without treatment in the majority of subjects. Approximately 19% received antihistamines and 5% received steroids, although the therapeutic benefit of these therapies is uncertain.

In the second part of this study after a 4 to 6 week wash out period, subjects developing a rash on FACTIVE were treated with ciprofloxacin (n=136) or placebo (n=50); 5.9% developed rash when treated with ciprofloxacin and 2.0% developed rash when treated with placebo. The cross sensitization rate to other fluoroquinolones was not evaluated in this clinical study. There was no evidence of sub-clinical sensitization to FACTIVE on a second exposure (i.e., subjects who had not developed a rash to FACTIVE in the first part of the study were not at higher risk of developing a rash to FACTIVE with a second exposure).

There was no relationship between the incidence of rash and systemic exposure (Cmax and AUC) to either gemifloxacin or its major metabolite, N-acetyl gemifloxacin.

REFERENCES

1. Clinical and Laboratory Standards Institute. Methods for Dilution Antimicrobial Susceptibility Tests for Bacteria that Grow Aerobically-Seventh Edition. Clinical and Laboratory Standards Institute document M7-A7, Vol. 26, No. 2, CLSI, Wayne, PA, January 2006.

2. Clinical and Laboratory Standards Institute. Performance Standards for Antimicrobial Disk Susceptibility Tests-Ninth Edition. Clinical and Laboratory Standards Institute document M2-A9, Vol. 26, No. 1, CLSI, Wayne, PA, January 2006.

DATE OF REVISION May 2016
© Merus Labs International Inc.
FACTIVE is a registered trademark of LG Life Sciences.
Rx only

Manufactured for:
Toronto, ON M5K 1H1 Canada

Licensed from LG Life Sciences, Ltd. Seoul, Korea

MRS-001-0313-03

MEDICATION GUIDE

FACTIVE® [FAC-tiv]
(gemifloxacin)
320mg Tablets

Read the Medication Guide that comes with FACTIVE before you start taking it and each time you get a refill. There may be new information. This Medication Guide does not take the place of talking to your healthcare provider about your medical condition or your treatment.

What is the most important information I should know about FACTIVE?

FACTIVE, a fluoroquinolone antibacterial medicine, can cause serious side effects. Some of these serious side effects can happen at the same time and could result in death.

If you get any of the following serious side effects while you are taking FACTIVE, you should stop taking FACTIVE immediately and get medical help right away.
1. Tendon rupture or swelling of the tendon (tendinitis)

- Tendon problems can happen in people of all ages who take FACTIVE.

Tendons are tough cords of tissue that connect muscles to bones.

-
  - Symptoms of tendon problems may include: Pain, swelling, tears, and inflammation of tendons including the back of the ankle (Achilles), shoulder, hand, or other tendon sites.

- The risk of getting tendon problems while you take FACTIVE is higher if you:
  - are over 60 years of age
  - are taking steroids (corticosteroids)
  - have had a kidney, heart or lung transplant.

Tendon problems can happen in people who do not have the above risk factors when they take FACTIVE.

- Other reasons that can increase your risk of tendon problems can include:
  - physical activity or exercise
  - kidney failure
  - tendon problems in the past, such as in people with rheumatoid arthritis (RA).
- Stop taking FACTIVE immediately and get medical help right away at the first sign of tendon pain, swelling or inflammation. Stop taking FACTIVE until tendinitis or tendon rupture has been ruled out by your healthcare provider. Avoid exercise and using the affected area. The most common area of pain and swelling is the Achilles tendon at the back of your ankle. This can also happen with other tendons.
- Talk to your healthcare provider about the risk of tendon rupture with continued use of FACTIVE. You may need a different antibiotic that is not a fluoroquinolone to treat your infection.
- Tendon rupture can happen while you are taking or after you have finished taking FACTIVE. Tendon ruptures can happen within hours or days of taking FACTIVE, and have happened up to several months after patients have finished taking their fluoroquinolone.
- Get medical help right away if you get any of the following signs or symptoms of a tendon rupture:
  - hear or feel a snap or pop in a tendon area
  - bruising right after an injury in a tendon area
  - unable to move the affected area or bear weight

2. Changes in sensation and possible nerve damage (Peripheral Neuropathy). Damage to the nerves in arms, hands, legs, or feet can happen in people taking fluoroquinolones, including FACTIVE. Stop FACTIVE and talk with your healthcare provider right away if you get any of the following symptoms of peripheral neuropathy in your arms, hands, legs, or feet:

- pain
- burning
- tingling
- numbness
- weakness

The nerve damage may be permanent.

3. Central Nervous System (CNS) Effects. Seizures have been reported in people who take fluoroquinolone antibiotics, including FACTIVE. Tell your healthcare provider if you have a history of seizures. Ask your healthcare provider whether taking FACTIVE will change your risk of having a seizure. Central Nervous System (CNS) side effects may happen as soon as after taking the first dose of FACTIVE. Talk to your healthcare provider right away if you get any of these side effects, or other changes in mood or behavior:

- feel dizzy
- seizures
- hear voices, see things, or sense things that are not there (hallucinations)
- feel restless
- tremors
- feel anxious or nervous
- confusion
- depression
- trouble sleeping
- feel more suspicious (paranoia)
- suicidal thoughts or acts
- nightmares

4. Worsening of myasthenia gravis (a disease which causes muscle weakness). Fluoroquinolones like FACTIVE may cause worsening of myasthenia gravis symptoms, including muscle weakness and breathing problems. Tell your healthcare provider if you have a history of myasthenia gravis before you start taking FACTIVE. Call your healthcare provider right away if you have any worsening muscle weakness or breathing problems.

See the section “ What are the possible side effects of FACTIVE?” for more information about side effects.

What is FACTIVE?

FACTIVE is a fluoroquinolone antibiotic medicine used to treat certain infections caused by certain germs called bacteria in adults 18 years or older. It is not known if FACTIVE is safe and works in children under 18 years of age. Children have a higher chance of getting bone, joint, or tendon (musculoskeletal) problems such as pain or swelling while taking fluoroquinolone antibiotic medicines.

Sometimes infections are caused by viruses rather than by bacteria. Examples include viral infections in the sinuses and lungs, such as the common cold or flu. Antibiotics including FACTIVE do not kill viruses.

Call your healthcare provider if you think your condition is not getting better while you are taking FACTIVE.

Who should not take FACTIVE?

Do not take FACTIVE if you have ever had a severe allergic reaction to an antibiotic known as a fluoroquinolone, or are allergic to any of the ingredients in FACTIVE. Ask your healthcare provider if you are not sure. See the list of ingredients in FACTIVE at the end of this Medication Guide.

What should I tell my healthcare provider before taking FACTIVE?

See “What is the most important information I should know about FACTIVE?”

Tell your healthcare provider about all your medical conditions, including if you:

- have tendon problems. FACTIVE should not be used in patients who have a history of tendon problems.
- have a disease that causes muscle weakness (myasthenia gravis). FACTIVE should not be used in patients who have a known history of myasthenia gravis.
- have central nervous system problems (such as epilepsy)
- have nerve problems. FACTIVE should not be used in patients who have a history of nerve problems called peripheral neuropathy.
- have or anyone in your family has an irregular heartbeat, especially a condition called “QT prolongation”
- have low blood potassium (hypokalemia) or magnesium (hypomagnesemia)
- have a slow heartbeat (bradycardia)
- have a history of seizures
- have kidney problems. You may need a lower dose of FACTIVE if your kidneys do not work well.
- have rheumatoid arthritis (RA) or other history of joint problems
- are pregnant or planning to become pregnant. It is not known if FACTIVE will harm your unborn child.
- are breast-feeding or planning to breast-feed. It is not known if FACTIVE passes into breast milk. You and your healthcare provider should decide whether you will take FACTIVE or breast-feed.

Tell your healthcare provider about all the medicines you take, including prescription and non-prescription medicines, vitamins, and herbal and dietary supplements. FACTIVE and other medicines can affect each other causing side effects. Especially tell your healthcare provider if you take:

- an NSAID (Non-Steroidal Anti-Inflammatory Drug). Many common medicines for pain relief are NSAIDs. Taking an NSAID while you take FACTIVE or other fluoroquinolones may increase your risk of central nervous system effects and seizures. See “ What are the possible side effects of FACTIVE?”
- a blood thinner (warfarin, Coumadin®, Jantoven®)
- a medicine to control your heart rate or rhythm (antiarrhythmics). See “ What are the possible side effects of FACTIVE? ”
- an anti-psychotic medicine
- a tricyclic antidepressant
- a water pill (diuretic)
- probenecid (Probalan, Col-Probenecid)
- a steroid medicine. Corticosteroids taken by mouth or by injection may increase the chance of tendon injury. See “ What is the most important information I should know about FACTIVE? ”
- Certain medicines may keep FACTIVE from working correctly. Take FACTIVE either 3 hours before or 2 hours after taking these products:
  - an antacid, multivitamin, or other product that contains magnesium, aluminum, iron, or zinc.
  - sucralfate (Carafate®).
  - didanosine (Videx®, Videx EC®).

Ask your healthcare provider if you are not sure if any of your medicines are listed above.

Know the medicines you take. Keep a list of your medicines and show it to your healthcare provider and pharmacist when you get a new medicine.

How should I take FACTIVE?

- Take FACTIVE exactly as prescribed by your healthcare provider.
- Take FACTIVE at about the same time each day.
- FACTIVE tablets should be swallowed.
- FACTIVE can be taken with or without food.
- FACTIVE should not be taken with dairy products (like milk or yogurt) or calcium-fortified juices alone, but may be taken with a meal that contains these products.
- Drink plenty of fluids while taking FACTIVE.
- Do not skip any doses, or stop taking FACTIVE even if you begin to feel better, until you finish your prescribed treatment, unless:
  - you have tendon effects (see “ What is the most important information I should know about FACTIVE? ”),
  - you have nerve problems (see " What is the most important information I should know about FACTIVE? ”),
  - you have central nervous system problems (see “ What is the most important information I should know about FACTIVE? ”),
  - you have a serious allergic reaction (see “ What are the possible side effects of FACTIVE? ”), or your healthcare provider tells you to stop.
- This will help make sure that all of the bacteria are killed and lower the chance that the bacteria will become resistant to FACTIVE. If this happens, FACTIVE and other antibiotic medicines may not work in the future.
- If you miss a dose of FACTIVE, take it as soon as you remember. Do not take more than 1 dose of FACTIVE in one day.
- If you take too much, call your healthcare provider or get medical help immediately.

What should I avoid while taking FACTIVE?

- FACTIVE can make you feel dizzy and lightheaded. Do not drive, operate machinery, or do other activities that require mental alertness or coordination until you know how FACTIVE affects you.
- Avoid sunlamps, tanning beds, and try to limit your time in the sun. FACTIVE can make your skin sensitive to the sun (photosensitivity) and the light from sunlamps and tanning beds. You could get severe sunburn, blisters or swelling of your skin. If you get any of these symptoms while taking FACTIVE, call your healthcare provider right away. You should use sunscreen and wear a hat and clothes that cover your skin if you have to be in sunlight.

What are the possible side effects of FACTIVE?

FACTIVE can cause side effects that may be serious or even cause death. See “ What is the most important information I should know about FACTIVE? ”

Other serious side effects of FACTIVE include:

- Serious allergic reactions

Allergic reactions can happen in people taking fluoroquinolones, including FACTIVE, even after only one dose. Stop taking FACTIVE and get emergency medical help right away if you get any of the following symptoms of a severe allergic reaction:

-
  - hives
  - trouble breathing or swallowing
  - swelling of the lips, tongue, face
  - throat tightness, hoarseness
  - rapid heartbeat
  - faint
- Yellowing of the skin or eyes

Stop taking FACTIVE and call your healthcare provider right away if you get yellowing of your skin or white part of your eyes, or if you have dark urine. These can be signs of a serious reaction to FACTIVE (a liver problem).

- Skin rash

Skin rash may happen in people taking FACTIVE. Stop taking FACTIVE at the first sign of a skin rash and call your healthcare provider. Skin rash may be a sign of a more serious reaction to FACTIVE. Rash happens more often with FACTIVE in:

-
  - women, especially women who take hormone replacement therapy
  - people under 40 years of age
  - people who take FACTIVE for longer than 5 days.
- Serious heart rhythm changes (QTc prolongation and torsades de pointes)
  Tell your healthcare provider right away if you have a change in your heartbeat (a fast or irregular heartbeat), or if you faint. FACTIVE may cause a rare heart problem known as prolongation of the QT interval. This condition can cause an abnormal heartbeat and can be very dangerous. The chances of this happening are higher in people:
  - who are elderly
  - with a family history of prolonged QT interval
  - with low blood potassium (hypokalemia)
  - who take certain medicines to control heart rhythm (antiarrhythmics).
- Intestine infection (Pseudomembranous colitis)

Pseudomembranous colitis can happen with most antibiotics, including FACTIVE. Call your healthcare provider right away if you get watery diarrhea, diarrhea that does not go away, or bloody stools. You may have stomach cramps and a fever. Pseudomembranous colitis can happen 2 or more months after you have finished your antibiotic.

- Sensitivity to sunlight (photosensitivity)

See “What should I avoid while taking FACTIVE?”

- Joint problems

The most common side effects of FACTIVE include:

- diarrhea
- rash
- nausea
- headache
- stomach pain
- vomiting
- dizziness

These are not all the possible side effects of FACTIVE. Tell your healthcare provider about any side effect that bothers you or that does not go away.

Call your doctor for medical advice about side effects. You may report side effects to FDA at 1-800-FDA-1088.

How should I store FACTIVE?

- Store FACTIVE at room temperature between 59º - 86ºF (15º to 30ºC).
- Keep FACTIVE away from light.

Keep FACTIVE and all medicines out of the reach of children.

General Information about FACTIVE

Medicines are sometimes prescribed for purposes other than those listed in a Medication Guide. Do not use FACTIVE for a condition for which it is not prescribed. Do not give FACTIVE to other people, even if they have the same symptoms that you have. It may harm them.

This Medication Guide summarizes the most important information about FACTIVE. If you would like more information about FACTIVE, talk with your healthcare provider. You can ask your healthcare provider or pharmacist for information about FACTIVE that is written for healthcare professionals. For more information go to www.FACTIVE.com or call 1-888-431-4276.

What are the ingredients in Factive?

- Active ingredient: gemifloxacin
- Inactive ingredients: crospovidone, hydroxypropyl methycellulose, magnesium stearate, microcrystalline cellulose, polyethylene glycol, povidone, titanium dioxide.

© Merus Labs International Inc.
FACTIVE is a registered trademark of LG Life Sciences.

Manufactured for:
Toronto, ON M5K 1H1 Canada

Licensed from LG Life Sciences, Ltd. Seoul, Korea

MRS-001-0313-03

This Medication Guide has been approved by the U.S. Food and Drug Administration.

Revised 07/2016

PACKAGE LABEL

Factive 5 Tablets

Factive 7 Tablets